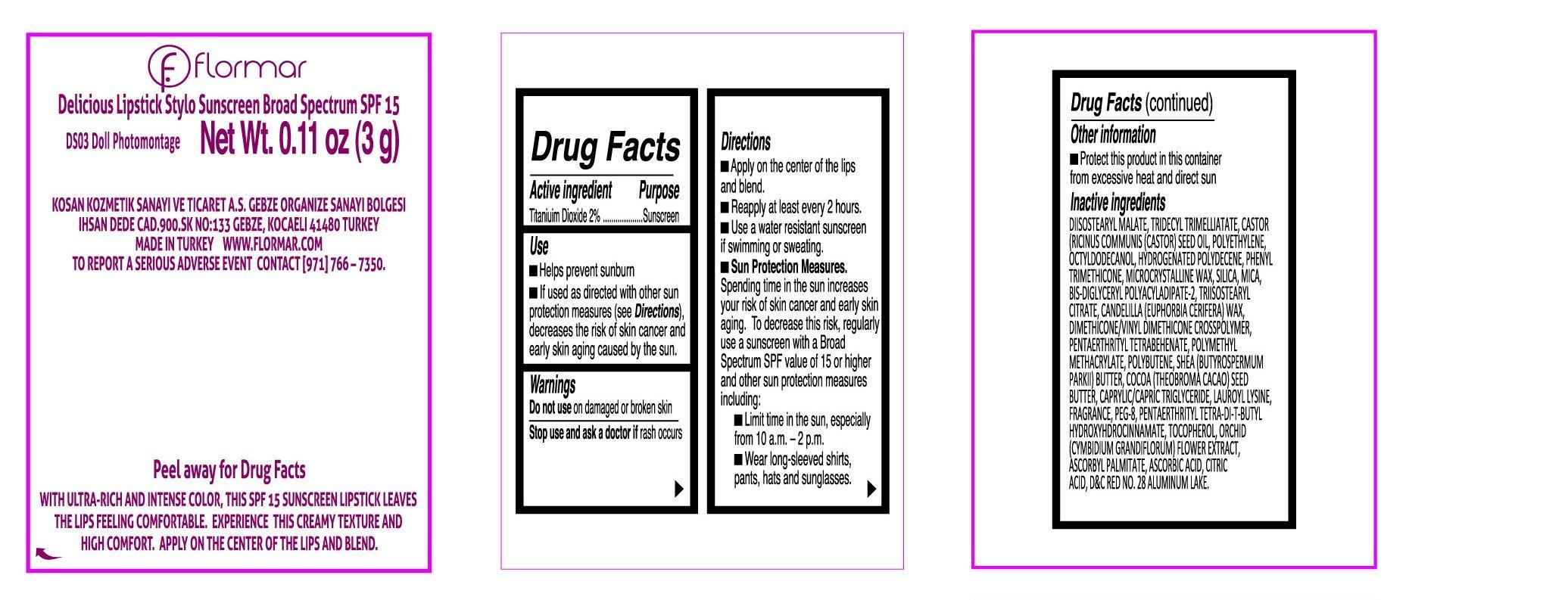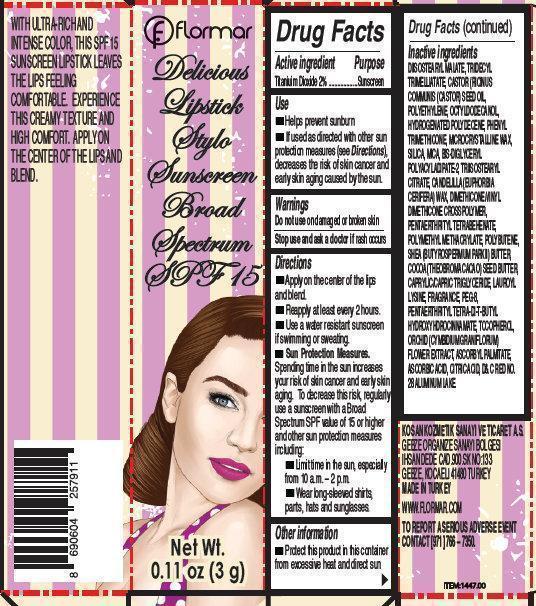 DRUG LABEL: flormar Delicious Lipstick Stylo Sunscreen Broad Spectrum SPF 15 DS03 Doll Photomontage
NDC: 61722-230 | Form: STICK
Manufacturer: Kosan Kozmetik Sanayi ve Ticaret A.S.
Category: otc | Type: HUMAN OTC DRUG LABEL
Date: 20191018

ACTIVE INGREDIENTS: TITANIUM DIOXIDE 20 mg/1 g
INACTIVE INGREDIENTS: DIISOSTEARYL MALATE; TRIDECYL TRIMELLITATE; CASTOR OIL; HIGH DENSITY POLYETHYLENE; OCTYLDODECANOL; PHENYL TRIMETHICONE; MICROCRYSTALLINE WAX; SILICON DIOXIDE; MICA; TRIISOSTEARYL CITRATE; CANDELILLA WAX; PENTAERYTHRITYL TETRABEHENATE; SHEA BUTTER; COCOA BUTTER; MEDIUM-CHAIN TRIGLYCERIDES; LAUROYL LYSINE; POLYETHYLENE GLYCOL 400; TOCOPHEROL; ASCORBYL PALMITATE; ASCORBIC ACID; CITRIC ACID MONOHYDRATE; D&C RED NO. 28

flormar Delicious Lipstick Stylo Sunscreen Broad Spectrum SPF 15 DS03 Doll Photomontage

Active ingredient

Titaniuim Dioxide 2%

Purpose

Sunscreen

Use

- Helps prevent sunburn
- If used as directed with other sun protection measures (see Directions), decreases the risk of skin cancer and early skin aging caused by the sun.

Warnings

Do not use

on damaged or broken skin

Stop use and ask a doctor if

rash occurs

Directions

- Apply on the center of the lips and blend
- Reapply at least every 2 hours.
- Use a water resistant sunscreen if swimming or sweating.
- Sun Protection Measures. Spending time in the sun increases your risk of skin cancer and early skin aging. To decrease this risk, regularly use a sunscreen with a Broad Spectrum SPF value of 15 or higher and other sun protection measures including:
- Limit time in the sun, especially from 10 a.m. - 2 p.m.
- Wear long-sleeved shirts, pants, hats and sunglasses

Other information

Protect this product in this container from excessive heat and direct sun

Inactive ingredients

DIISOSTEARYL MALATE, TRIDECYL TRIMELLIATATE, CASTOR (RICINUS COMMUNIS (CASTOR) SEED OIL, POLYETHYLENE, OCTYLDODECANOL,
HYDROGENATED POLYDECENE, PHENYL TRIMETHICONE, MICROCRYSTALLINE WAX, SILICA, MICA, BIS-DIGLYCERYL POLYACYLADIPATE-2, TRIISOSTEARYL CITRATE, CANDELILLA (EUPHORBIA CERIFERA) WAX, DIMETHICONE/VINYL DIMETHICONE CROSSPOLYMER, PENTAERTHRITYL TETRABEHENATE, POLYMETHYL METHACRYLATE, POLYBUTENE, SHEA (BUTYROSPERMUM PARKII) BUTTER, COCOA (THEOBROMA CACAO) SEED BUTTER, CAPRYLIC/CAPRIC TRIGLYCERIDE, LAUROYL LYSINE, FRAGRANCE, PEG-8, PENTAERTHRITYL TETRA-DI-T-BUTYL
HYDROXYHDROCINNAMATE, TOCOPHEROL, ORCHID (CYMBIDIUM GRANIFLORUM) FLOWER EXTRACT, ASCORBYL PALMITATE, ASCORBIC ACID, CITRIC ACID, D& C RED NO. 28 ALUMINUM LAKE.

KOSAN KOZMETIK SANAYI VE TICARET A.S.

GEBZE ORGANIZE SANAYI BOLGESI IHSAN DEDE CAD.900.SK NO:133 GEBZE, KOCAELI 41480 TURKEY
MADE IN TURKEY
WWW.FLORMAR.COM
TO REPORT A SERIOUS ADVERSE EVENT
CONTACT [971] 766 – 7350. WITH ULTRA-RICH AND INTENSE COLOR, THIS SPF 15 SUNSCREEN LIPSTICK LEAVES THE LIPS FEELING
COMFORTABLE. EXPERIENCE THIS CREAMY TEXTURE AND HIGH COMFORT. APPLY ON THE CENTER OF THE LIPS AND BLEND.

Product Labels

flormar Delicious Lipstick Style Sunscreen Broad Spectrum SPF 15 Net Wt. 0.11 oz (3g)